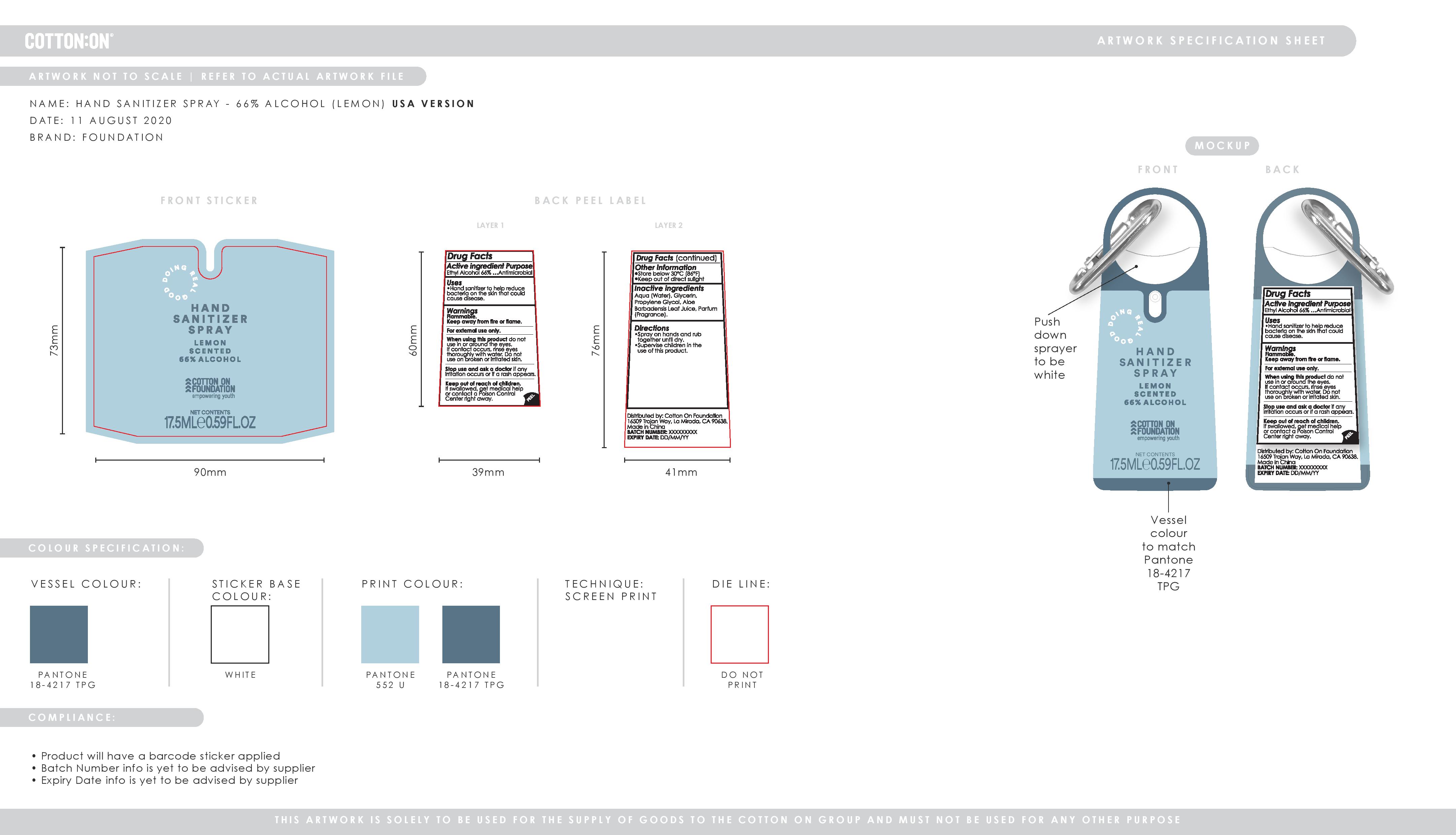 DRUG LABEL: Hand Sanitizer
NDC: 90015-004 | Form: SPRAY
Manufacturer: COTTON ON USA INC.
Category: otc | Type: HUMAN OTC DRUG LABEL
Date: 20201006

ACTIVE INGREDIENTS: ALCOHOL 66.4 mL/100 mL
INACTIVE INGREDIENTS: ALOE VERA LEAF 0.05 mL/100 mL; GLYCERIN 0.5 mL/100 mL; PROPYLENE GLYCOL 0.5 mL/100 mL; WATER 32.58 mL/100 mL

FOUNDATION 2020 Q2 HAND SANITIZER ALCOHOL USA 66
Citrus - Blue

Active Ingredient(s)

Ethyl Alcohol 66% ... Purpose: Antimicrobial

Purpose

Antimicrobial, Hand Sanitizer

Use

Hand Sanitizer to help reduce bacteria on the skin that could cause disease.

Warnings

Flammable. For external use only. Keep away from heat or flame

Do not use

When using this product do not use in or around the eyes. If contact occurs, rinse eyes thoroughly with water. Do not use on broken or irritated skin.

When using this product do not use in or around the eyes. If contact occurs, rinse eyes thoroughly with water. Do not use on broken or irritated skin.

Stop use and ask a doctor if irritation or rash occurs.

Keep out of reach of children. If swallowed, get medical help or contact a Poison Control Center right away.

Other information

- Store below 30C (86F)
- Keep out of direct sunlight

Inactive ingredients

Water (aqua), Glycerin, Propylene Glycol, Aloe Barbadensis Leaf Juice, Fragrance

DIRECTIONS

Dirctions

- Spray on hands and rub together until dry.
- Supervise children in the use of this product.

Package Label - Principal Display Panel

17.5 mL NDC: 90015-004-01